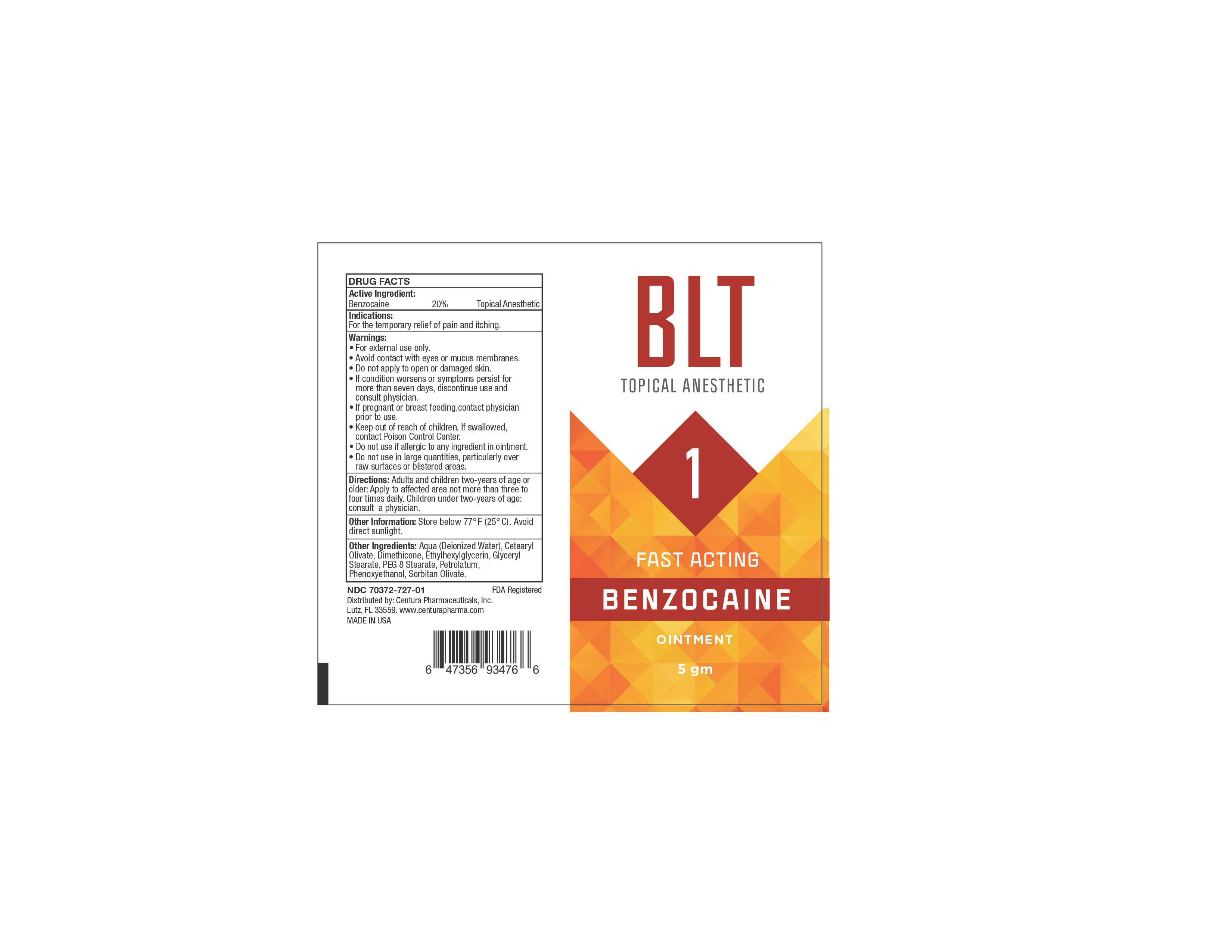 DRUG LABEL: BLT 1
NDC: 70372-727 | Form: OINTMENT
Manufacturer: CENTURA PHARMACEUTICALS INC
Category: otc | Type: HUMAN OTC DRUG LABEL
Date: 20260115

ACTIVE INGREDIENTS: BENZOCAINE 20 g/100 g
INACTIVE INGREDIENTS: PEG-100 STEARATE; PHENOXYETHANOL; DIMETHICONE; WATER; CETEARYL OLIVATE; ETHYLHEXYLGLYCERIN; GLYCERYL STEARATE SE; PEG-8 STEARATE; PETROLATUM; SORBITAN OLIVATE

ACTIVE INGREDIENT

Benzocaine 20%

PURPOSE

Topical Anesthetic

USES

For the temporary relief of pain and itching.

WARNINGS

• For external use only.
• Avoid contact with eyes or mucus membranes.
• Do not apply to open or damaged skin.
• If condition worsens or symptoms persist for
more than seven days, discontinue use and
consult physician.
• If pregnant or breast feeding,contact physician
prior to use.
• Keep out of reach of children. If swallowed,
contact Poison Control Center.
• Do not use if allergic to any ingredient in ointment.
• Do not use in large quantities, particularly over
raw surfaces or blistered areas.

DIRECTIONS

Adults and children two-years of age or older: Apply to affected area not more than three to four times daily. Children under two-years of age: consult a physician

OTHER INFORMATION

Store below 77° F (25° C). Avoid
direct sunlight.